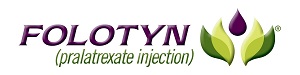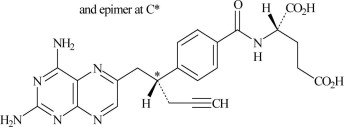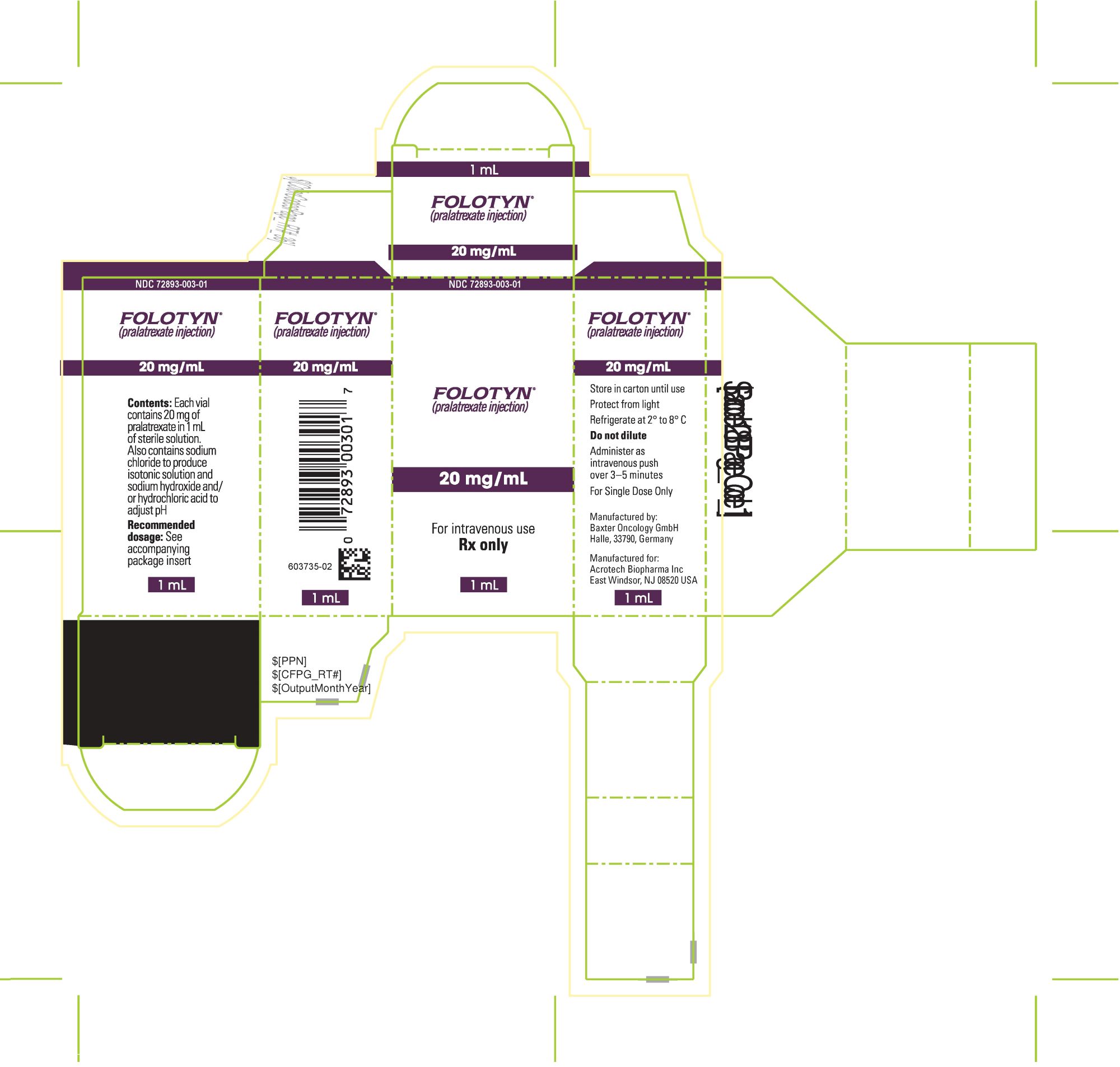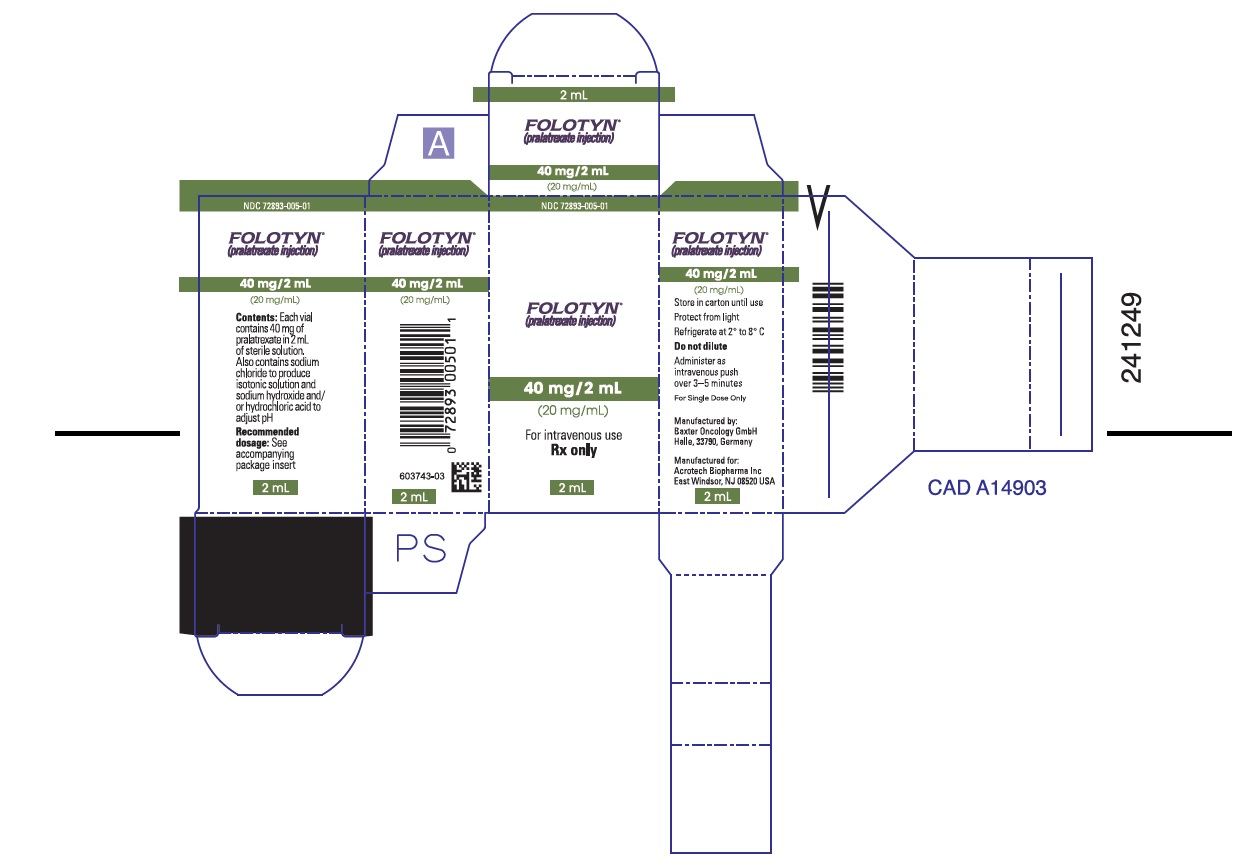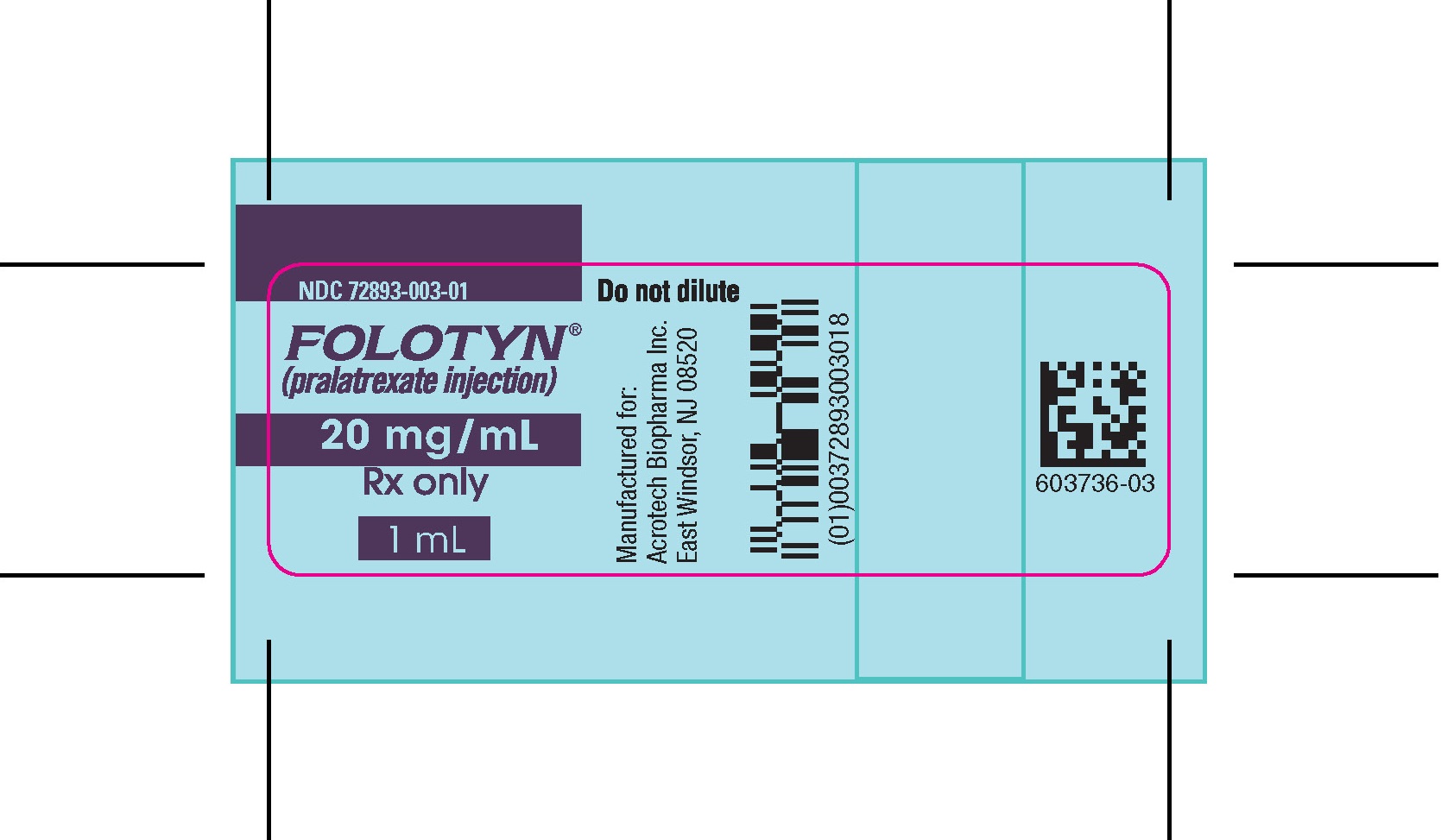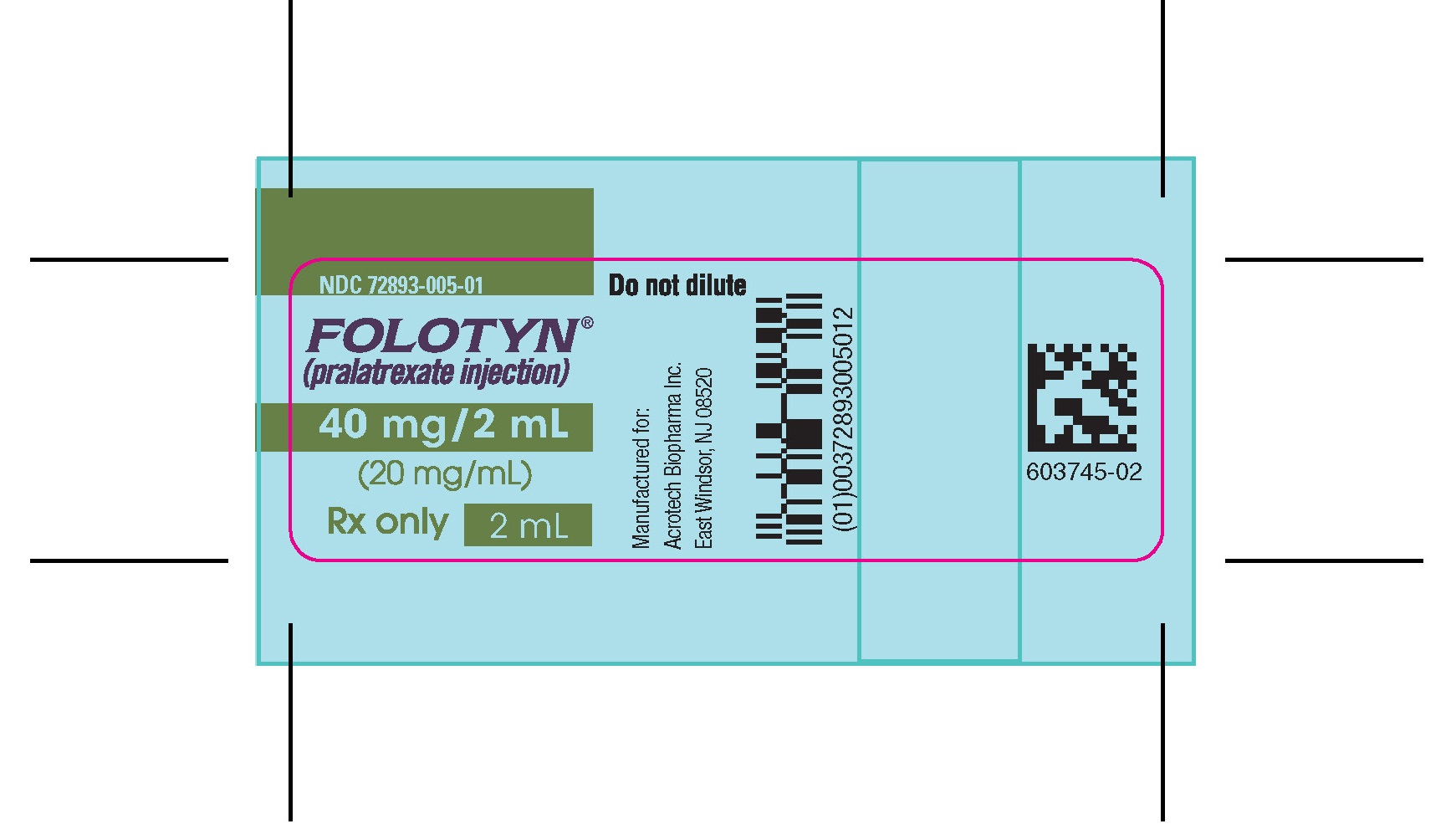 DRUG LABEL: Folotyn
NDC: 72893-003 | Form: INJECTION
Manufacturer: Acrotech Biopharma Inc
Category: prescription | Type: Human Prescription Drug Label
Date: 20240926

ACTIVE INGREDIENTS: PRALATREXATE 20 mg/1 mL
INACTIVE INGREDIENTS: SODIUM CHLORIDE; SODIUM HYDROXIDE; HYDROCHLORIC ACID; WATER

HIGHLIGHTS OF PRESCRIBING INFORMATION

These highlights do not include all the information needed to use FOLOTYN® safely and effectively. See full prescribing information for FOLOTYN.
FOLOTYN (pralatrexate injection), for intravenous use
Initial U.S. Approval: 2009

1 INDICATIONS AND USAGE

FOLOTYN is a dihydrofolate reductase inhibitor indicated for the treatment of patients with relapsed or refractory peripheral T-cell lymphoma (PTCL).
This indication is approved under accelerated approval based on overall response rate. Continued approval for this indication may be contingent upon verification and description of clinical benefit in a confirmatory trial(s). (1)

2 DOSAGE AND ADMINISTRATION

- Supplement patients with vitamin B12 mg intramuscularly every 8-10 weeks starting 10 weeks before the first dose and folic acid 1 to 1.25 mg orally once daily starting 10 days before the first dose. (2.1)
- The recommended dosage of FOLOTYN is 30 mg/m^2 intravenously over 3 to 5 minutes once weekly for 6 weeks in 7-week cycles. (2.1)
- For patients with severe renal impairment (GFR 15 to 29 mL/min/1.73 m^2), reduce the FOLOTYN dose to 15 mg/m^2 (2.1).

3 DOSAGE FORMS AND STRENGTHS

Injection: 20 mg/1 mL or 40 mg/2 mL in a single-dose vial (3)

4 CONTRAINDICATIONS

None.(4)

5 WARNINGS AND PRECAUTIONS

- Myelosuppression: Monitor complete blood counts and omit and/or reduce dose based on ANC and platelet count. (2.4, 5.1)
- Mucositis: Monitor at least weekly. Omit and/or reduce dose for grade 2 or higher mucositis. (2.4, 5.2)
- Dermatologic reactions: Reactions, including fatal reactions, occurred and may be progressive and increase in severity with further treatment. Monitor closely and withhold or discontinue FOLOTYN based on severity. (2.4, 5.3)
- Tumor lysis syndrome: Monitor patients who are increased risk and treat promptly. (5.4)
- Hepatic toxicity: Monitor for liver function tests. Omit until recovery, adjust or discontinue therapy based on severity. (2.4, 5.5)
- Risk of increased toxicity with renal impairment: Avoid FOLOTYN in patients with end stage renal disease with or without dialysis. If the potential benefit of administration justifies the potential risk, monitor renal function and reduce the FOLOTYN dose based on adverse reactions. (2.3, 2.4, 5.6)
- Embryo-fetal toxicity: Can cause fetal harm. Advise patients of the potential risk to a fetus and to use an effective method of contraception. (5.7, 8.1, 8.3)

6 ADVERSE REACTIONS

Most common adverse reactions (>35%) are mucositis, thrombocytopenia, nausea, and fatigue. (6.1)

To report SUSPECTED ADVERSE REACTIONS, contact Acrotech Biopharma Inc at 1-888-255-6788 or www.FOLOTYN.com or FDA at 1-800-FDA-1088 or www.fda.gov/medwatch

7 DRUG INTERACTIONS

- Avoid coadministration with probenecid or nonsteroidal anti-inflammatory drugs. If coadministration is unavoidable, monitor for increased risk of adverse reactions. (7.1)

8 USE IN SPECIFIC POPULATIONS

- Lactation: Advise not to breastfeed. (8.2)

FULL PRESCRIBING INFORMATION

1 INDICATIONS AND USAGE

FOLOTYN is indicated for the treatment of patients with relapsed or refractory peripheral T-cell lymphoma (PTCL).

This indication is approved under accelerated approval based on overall response rate [see Clinical Studies (14)]. Continued approval for this indication may be contingent upon verification and description of clinical benefit in a confirmatory trial(s).

2 DOSAGE AND ADMINISTRATION

2.1 Important Dosing Information

Pretreatment Vitamin Supplementation

Folic Acid
Instruct patients to take folic acid 1 to 1.25 mg orally once daily beginning 10 days before the first dose of FOLOTYN. Continue folic acid during treatment with FOLOTYN and for 30 days after the last dose [see Warnings and Precautions (5.1, 5.2)].

Vitamin B12
Administer vitamin B12 1 mg intramuscularly within 10 weeks prior to the first dose of FOLOTYN and every 8-10 weeks thereafter. Subsequent vitamin B12 injections may be given the same day as treatment with FOLOTYN [see Warnings and Precautions (5.1, 5.2)].

2.2 Recommended Dosage

The recommended dosage of FOLOTYN is 30 mg/m^2 intravenously over 3-5 minutes once weekly for 6 weeks in 7-week cycles until progressive disease or unacceptable toxicity.

2.3 Dosage Modifications for Renal Impairment and End Stage Renal Disease

- Severe renal impairment (eGFR 15 to 29 mL/min/1.73 m^2 by MDRD): Reduce the FOLOTYN dose to 15 mg/m^2 [see Use in Specific Populations (8.6)].
- End stage renal disease (ESRD: eGFR less than 15 mL/min/1.73 m^2 by MDRD) with or without dialysis: Avoid administration. If the potential benefit of administration justifies the potential risk, monitor renal function and reduce the FOLOTYN dose based on adverse reactions [see Warnings and Precautions (5.6), Use in Specific Populations (8.6)].

2.4 Monitoring and Dosage Modifications for Adverse Reactions

Monitoring
Monitor complete blood cell counts and severity of mucositis at baseline and weekly. Perform serum chemistry tests, including renal and hepatic function, prior to the start of the first and fourth dose of each cycle.

Recommended Dosage Modifications
Do not administer FOLOTYN until:

- Mucositis Grade 1 or less.
- Platelet of 100,000/mcL or greater for first dose and 50,000/mcL or greater for all subsequent doses.
- Absolute neutrophil count (ANC) of 1,000/mcL or greater.

Dosage modifications for adverse reactions are provided in Tables 1, 2, and 3.

Table 1 FOLOTYN Dose Modifications for Mucositis
Mucositis Gradea on Day of Treatment | Action | Recommended Dose upon Recovery to Grade 0 or 1
Mucositis Gradea on Day of Treatment | Action | Patients Without Severe Renal Impairment | Patients with Severe Renal Impairment
Grade 2 | Omit dose | Continue prior dose | Continue prior dose
Grade 2 recurrence | Omit dose | 20 mg/m^2 | 10 mg/m^2
Grade 3 | Omit dose | 20 mg/m^2 | 10 mg/m^2
Grade 4 | Stop therapy

a Based National Cancer Institute Common Terminology Criteria for Adverse Events (NCI CTCAE version 3.0)

Table 2 FOLOTYN Dosage Modifications for Myelosuppression
Blood Count on Day of Treatment | Duration of Toxicity | Action | Recommended Dose Upon Recovery
Blood Count on Day of Treatment | Duration of Toxicity | Action | Patients Without Severe Renal Impairment | Patients with Severe Renal Impairment
Platelet less than 50,000/mcL | 1 week | Omit dose | Continue prior dose | Continue prior dose
Platelet less than 50,000/mcL | 2 weeks | Omit dose | 20 mg/m^2 | 10 mg/m^2
Platelet less than 50,000/mcL | 3 weeks | Stop therapy
ANC 500 to 1,000/mcL and no fever | 1 week | Omit dose | Continue prior dose | Continue prior dose
ANC 500 to 1,000/mcL with fever or ANC less than 500/mcL | 1 week | Omit dose, give G‑CSF or GM‑CSF | Continue prior dose with G-CSF or GM‑CSF | Continue prior dose with G-CSF or GM‑CSF support
ANC 500 to 1,000/mcL with fever or ANC less than 500/mcL | 2 weeks or recurrence | Omit dose, give G‑CSF or GM‑CSF | 20 mg/m^2 with G-CSF or GM-CSF | 10 mg/m^2 with G-CSF or GM-CSF
ANC 500 to 1,000/mcL with fever or ANC less than 500/mcL | 3 weeks or 2nd recurrence | Stop therapy

G-CSF=granulocyte colony-stimulating factor; GM-CSF=granulocyte macrophage colony-stimulating factor

Table 3 FOLOTYN Dosage Modifications for All Other Adverse Reactions
Toxicity Grade a on Day of Treatment | Action | Recommended Dose upon Recovery to Grade 2 or Lower
Toxicity Grade a on Day of Treatment | Action | Patients Without Severe Renal Impairment | Patients with Severe Renal Impairment
Grade 3 | Omit dose | 20 mg/m^2 | 10 mg/m^2
Grade 4 | Stop therapy

a Based on NCI CTCAE version 3.0

2.5 Preparation and Administration

Parenteral drug products should be inspected visually for particulate matter and discoloration prior to administration, whenever solution and container permit. Do not use any vials exhibiting particulate matter or discoloration.

FOLOTYN is a hazardous drug. Follow applicable special handling and disposal procedures.^1 If FOLOTYN comes in contact with the skin, immediately and thoroughly wash with soap and water. If FOLOTYN
comes in contact with mucous membranes, flush thoroughly with water.

Aseptically withdraw the calculated dose from the appropriate number of vial(s) into a syringe for immediate use. Do not dilute FOLOTYN.

Administer undiluted FOLOTYN intravenously over 3-5 minutes via the side port of a free-flowing 0.9% Sodium Chloride Injection.

After withdrawal of dose, discard vial(s) including any unused portion.

3 DOSAGE FORMS AND STRENGTHS

Injection: 40 mg/2 mL (20 mg/mL) and 20 mg/mL clear yellow sterile solution in single-dose vial

4 CONTRAINDICATIONS

None

5 WARNINGS AND PRECAUTIONS

5.1 Myelosuppression

FOLOTYN can cause myelosuppression, manifested by thrombocytopenia, neutropenia, and/or anemia.

Administer vitamin B12 and instruct patients to take folic acid to reduce the risk of treatment-related myelosuppression [see Dosage and Administration (2.1)].

Monitor complete blood counts and omit and/or reduce the dose based on ANC and platelet count prior to each dose [see Dosage and Administration (2.4)].

5.2 Mucositis

FOLOTYN can cause mucositis [see Adverse Reactions (6.1)].

Administer vitamin B12 and instruct patients to take folic acid to reduce the risk of mucositis [see Dosage and Administration (2.1)].

Monitor for mucositis weekly and omit and/or reduce the dose for grade 2 or higher mucositis [see Dosage and Administration (2.4)].

5.3 Dermatologic Reactions

FOLOTYN can cause severe dermatologic reactions, which may result in death. These dermatologic reactions have been reported in clinical studies (2.1% of 663 patients) and post marketing experience, and have included skin exfoliation, ulceration, and toxic epidermal necrolysis (TEN) [see Adverse Reactions (6.1, 6.2)]. They may be progressive and increase in severity with further treatment and may involve skin and subcutaneous sites of known lymphoma.

Monitor closely for dermatologic reactions. Withhold or discontinue FOLOTYN based on severity [see Dosage and Administration (2.4)].

5.4 Tumor Lysis Syndrome

FOLOTYN can cause tumor lysis syndrome (TLS). Monitor patients who are at increased risk of TLS and treat promptly.

5.5 Hepatic Toxicity

FOLOTYN can cause hepatic toxicity and liver function test abnormalities [see Adverse Reactions (6.1)]. Persistent liver function test abnormalities may be indicators of hepatic toxicity and require dose modification or discontinuation.

Monitor liver function tests. Omit dose until recovery, adjust or discontinue therapy based on the severity of the hepatic toxicity [see Dosage and Administration (2.4)].

5.6 Risk of Increased Toxicity with Renal Impairment

Patients with severe renal impairment (eGFR 15 to < 30 mL/min/1.73 m^2 based on MDRD) may be at greater risk for increased exposure and adverse reactions. Reduce FOLOTYN dosage in patients with severe renal impairment [see Dosage and Administration (2.3)].

Serious adverse reactions, including TEN and mucositis, were reported in patients with end stage renal disease (ESRD) undergoing dialysis who were administered FOLOTYN. Avoid FOLOTYN in patients with ESRD with or without dialysis. If the potential benefit of administration justifies the potential risk, monitor renal function and reduce the FOLOTYN dose based on adverse reactions [see Dosage and Administration (2.3)].

5.7 Embryo-Fetal Toxicity

Based on findings in animals and its mechanism of action, FOLOTYN can cause fetal harm when administered to a pregnant woman. FOLOTYN was embryotoxic and fetotoxic in rats and rabbits. Advise pregnant women of the potential risk to a fetus. Advise females of reproductive potential to use effective contraception during treatment with FOLOTYN and for 6 months after the last dose. Advise males with female partners of reproductive potential to use effective contraception during treatment with FOLOTYN and for 3 months after the last dose [see Use in Specific Populations (8.1, 8.3)].

6 ADVERSE REACTIONS

The following clinically significant adverse reactions are described elsewhere in the labeling:

- Myelosuppression [see Warnings and Precautions (5.1)]
- Mucositis [see Warnings and Precautions (5.2)]
- Dermatologic Reactions [see Warnings and Precautions (5.3)]
- Tumor Lysis Syndrome [see Warnings and Precautions (5.4)]
- Hepatic Toxicity [see Warnings and Precautions (5.5)]

6.1 Clinical Trials Experience

Because clinical studies are conducted under widely varying conditions, adverse reaction rates observed in the clinical studies of a drug cannot be directly compared to rates in the clinical studies of another drug and may not reflect the rates observed in practice.

Peripheral T-cell Lymphoma

The safety of FOLOTYN was evaluated in Study PDX-008 [see Clinical Studies (14)]. Patients received FOLOTYN 30 mg/m^2 once weekly for 6 weeks in 7-week cycles. The median duration of treatment was 70 days (range: 1 day to 1.5 years). The majority of patients (69%, n = 77) remained at the target dose for the duration of treatment. Overall, 85% of scheduled doses were administered.

Forty-four percent of patients (n = 49) experienced a serious adverse event while on study or within 30 days after their last dose of FOLOTYN. The most common serious adverse events (> 3%), regardless of causality, were pyrexia, mucositis, sepsis, febrile neutropenia, dehydration, dyspnea, and thrombocytopenia. One death from cardiopulmonary arrest in a patient with mucositis and febrile neutropenia was reported in this trial. Across clinical trials, deaths from mucositis, febrile neutropenia, sepsis, and pancytopenia occurred in 1.2% of patients who received doses ranging from 30 mg/m^2 to 325 mg/m^2.

Twenty-three percent of patients (n = 25) discontinued treatment with FOLOTYN due to adverse reactions. The most frequent adverse reactions reported as the reason for discontinuation of treatment were mucositis (6%) and thrombocytopenia (5%).

The most common adverse reactions (> 35%) were mucositis, thrombocytopenia, nausea, and fatigue.

Table 4 summarizes the adverse reactions in Study PDX-008.

Table 4 Adverse Reactions in (≥ 10%) in Patients Who Received FOLOTYN in Study PDX-008
 | FOLOTYN N=111
 | All Grades (%) | Grade 3 (%) | Grade 4 (%)
Any Adverse Event | 100 | 43 | 31
Mucositisa | 70 | 17 | 4
Thrombocytopeniab | 41 | 14 | 19b
Nausea | 40 | 4 | 0
Fatigue | 36 | 5 | 2
Anemia | 34 | 15 | 2
Constipation | 33 | 0 | 0
Pyrexia | 32 | 1 | 1
Edema | 30 | 1 | 0
Cough | 28 | 1 | 0
Epistaxis | 26 | 0 | 0
Vomiting | 25 | 2 | 0
Neutropenia | 24 | 13 | 7
Diarrhea | 21 | 2 | 0
Dyspnea | 19 | 7 | 0
Hypokalemia | 15 | 4 | 1
Anorexia | 15 | 3 | 0
Rash | 15 | 0 | 0
Pruritus | 14 | 2 | 0
Pharyngolaryngeal pain | 14 | 1 | 0
Liver function test abnormalc | 13 | 5 | 0
Abdominal pain | 12 | 4 | 0
Pain in extremity | 12 | 0 | 0
Leukopenia | 11 | 3 | 4
Back pain | 11 | 3 | 0
Night sweats | 11 | 0 | 0
Asthenia | 10 | 1 | 0
Upper respiratory tract infection | 10 | 1 | 0
Tachycardia | 10 | 0 | 0

aMucositis includes stomatitis or mucosal inflammation of the gastrointestinal and genitourinary tracts.

bFive patients with platelets < 10,000/mcL

cLiver function test abnormal includes increased ALT, increased AST, and increased transaminases

6.2 Postmarketing Experience

The following adverse reactions have been identified during postapproval use of FOLOTYN. Because these reactions are reported voluntarily from a population of uncertain size, it is not always possible to reliably estimate their frequency or establish a causal relationship to drug exposure.

Dermatologic Reactions: Toxic epidermal necrolysis.

7 DRUG INTERACTIONS

7.1 Effects of Other Drugs on FOLOTYN

Coadministration of FOLOTYN with probenecid increased pralatrexate plasma concentrations [see Clinical Pharmacology (12.3)], which may increase the risk of adverse reactions. Avoid coadministration with probenecid or nonsteroidal anti-inflammatory drugs. If coadministration is unavoidable, monitor for increased risk of adverse reactions.

8 USE IN SPECIFIC POPULATIONS

8.1 Pregnancy

Risk Summary
Based on findings from animal studies and its mechanism of action [see Clinical Pharmacology (12.1)], FOLOTYN can cause fetal harm when administered to a pregnant woman. There are insufficient data on FOLOTYN use in pregnant women to evaluate for a drug- associated risk. FOLOTYN was embryotoxic and fetotoxic in rats and rabbits when administered during organogenesis at doses about 1.2% (0.012 times) of the clinical dose on a mg/m^2 basis. Advise pregnant women of the potential risk to a fetus.

The estimated background risk of major birth defects and miscarriage for the indicated population(s) is unknown. All pregnancies have a background risk of birth defect, loss, or other adverse outcomes. In the U.S. general population, the estimated background risk of major birth defects and miscarriage in clinically recognized pregnancies is 2-4% and 15-20%, respectively.

Data

Animal Data
Pralatrexate was embryotoxic and fetotoxic in rats at intravenous doses of 0.06 mg/kg/day (0.36 mg/m^2/day or about 1.2% of the clinical dose on a mg/m^2 basis) given on gestation days 7 through 20. Treatment with pralatrexate caused a dose-dependent decrease in fetal viability manifested as an increase in late, early, and total resorptions. There was also a dose-dependent increase in post-implantation loss. In rabbits, intravenous doses of 0.03 mg/kg/day (0.36 mg/m^2/day) or greater given on gestation days 8 through 21 also caused abortion and fetal lethality. This toxicity manifested as early and total resorptions, post-implantation loss, and a decrease in the total number of live fetuses.

8.2 Lactation

Risk Summary
There is no data on the presence of pralatrexate in human milk or its effects on the breastfed child or milk production. Because of the potential for serious adverse reactions in a breastfed child, advise women not to breastfeed during treatment with FOLOTYN and for 1 week after the last dose.

8.3 Females and Males of Reproductive Potential

FOLOTYN can cause fetal harm when administered to a pregnant woman [see Use in Specific Populations (8.1)].

Pregnancy Testing

Verify pregnancy status in females of reproductive potential prior to initiation of FOLOTYN.

Contraception

Females
Advise females of reproductive potential to use effective contraception during treatment with FOLOTYN and for 6 months following the last dose.

Males
Advise males with female partners of reproductive potential to use effective contraception during treatment with FOLOTYN and for 3 months following the last dose.

8.4 Pediatric Use

The safety and effectiveness of FOLOTYN in pediatric patients have not been established.

8.5 Geriatric Use

In the Study PDX-008, 36% of patients (n = 40) were 65 years of age and over. No overall differences in efficacy and safety were observed in patients based on age (< 65 years compared with ≥ 65 years). Due to the contribution of renal excretion to overall clearance of pralatrexate (approximately 34%), age-related decline in renal function may lead to a reduction in clearance and a commensurate increase in plasma exposure. In general, dose selection for an elderly patient should be cautious, reflecting the greater frequency of decreased hepatic, renal, or cardiac function, and of concomitant disease or other drug therapy. Since elderly patients may be at higher risk, monitor more closely. Omit dose and subsequently adjust or discontinue therapy for adverse reactions [see Dosage and Administration (2.4)].

8.6 Renal Impairment

No dosage modification is recommended for patients with mild or moderate renal impairment (eGFR 30 to 59 mL/min/1.73 m^2 based on MDRD). For patients with severe renal impairment (eGFR 15 to 29 mL/min/1.73 m^2), reduce the recommended dose of FOLOTYN [see Dosage and Administration (2.3)].

Serious adverse drug reactions, including TEN and mucositis, have been reported in patients with ESRD undergoing dialysis. Avoid the use of FOLOTYN in patients with ESRD with or without dialysis. If the potential benefit of administration justifies the potential risk, monitor renal function and reduce the FOLOTYN dose based on adverse reactions [see Dosage and Administration (2.3), Warnings and Precautions (5.6)].

10 OVERDOSAGE

No specific information is available on the treatment of overdosage of FOLOTYN. If an overdose occurs, general supportive measures should be instituted as deemed necessary by the treating healthcare provider. Based on FOLOTYN's mechanism of action, consider the prompt administration of leucovorin.

11 DESCRIPTION

Pralatrexate is a dihydrofolate reductase inhibitor. Pralatrexate has the chemical name (2S)-2-[[4-[(1RS)-1-[(2, 4-diaminopteridin-6-yl)methyl]but-3- ynyl]benzoyl]amino]pentanedioic acid. The molecular formula is C23H23N7O5 and the molecular weight is 477.48 g/mol. Pralatrexate is a 1:1 racemic mixture of S- and R- diastereomers at the C10 position (indicated with *). The structural formula is as follows:

Pralatrexate is an off-white to yellow solid. It is soluble in aqueous solutions at pH 6.5 or higher. Pralatrexate is practically insoluble in chloroform and ethanol. The pKa values are 3.25, 4.76, and 6.17.

FOLOTYN (pralatrexate) is supplied as a preservative-free, sterile, isotonic, non-pyrogenic clear yellow aqueous solution contained in a clear glass single-dose vial (Type I) for intravenous use. Each 1 mL of solution contains 20 mg of pralatrexate, sufficient sodium chloride to achieve an isotonic (280-300 mOsm) solution, and sufficient sodium hydroxide, and hydrochloric acid if needed, to adjust and maintain the pH at 7.5-8.5. FOLOTYN is supplied as either 20 mg (1 mL) or 40 mg (2 mL) single-dose vials at a concentration of 20 mg/mL.

12 CLINICAL PHARMACOLOGY

12.1 Mechanism of Action

Pralatrexate is a folate analog metabolic inhibitor that competitively inhibits dihydrofolate reductase. It is also a competitive inhibitor for polyglutamylation by the enzyme folylpolyglutamyl synthetase. This inhibition results in the depletion of thymidine and other biological molecules the synthesis of which depends on single carbon transfer.

12.2 Pharmacodynamics

Pralatrexate exposure-response relationship and the time course of pharmacodynamics responses are unknown.

12.3 Pharmacokinetics

Pralatrexate is a racemic mixture of S- and R-diastereomers. The pharmacokinetics of pralatrexate at the recommended dosage of 30 mg/m^2 once weekly have been evaluated in 10 patients with PTCL. Pralatrexate total systemic exposure (AUC) and maximum plasma concentration (Cmax) increased proportionally over a dose range 30 to 325 mg/m^2 (10.8 times the approved recommended dosage). No accumulation of pralatrexate was observed.

Distribution
Steady-state volume of distribution of pralatrexate S- and R-diastereomers is 105 L and 37 L, respectively. Protein binding of pralatrexate is approximately 67% in vitro.

Elimination
The total systemic clearance of pralatrexate diastereomers was 417 mL/min (S-diastereomer) and 191 mL/min (R-diastereomer). The terminal elimination half-life of pralatrexate was 12-18 hours (coefficient of variance [CV] = 62-120%).

Metabolism
Pralatrexate is not significantly metabolized by CYP450 isozymes or glucuronidases in vitro.

Excretion
Following a single dose of FOLOTYN 30 mg/m^2, approximately 34% of the pralatrexate dose was excreted unchanged into urine. Following a radiolabeled pralatrexate dose, 39% (CV = 28%) of the dose was recovered in urine as unchanged pralatrexate and 34% (CV = 88%) in feces as unchanged pralatrexate and/or any metabolites. 10% (CV = 95%) of the dose was exhaled over 24 hours.

Specific Populations
No clinically meaningful effect on the pharmacokinetics of pralatrexate was observed based on sex. The effect of hepatic impairment on the pharmacokinetics of pralatrexate has not been studied.

Patients with Renal Impairment
Following administration of a single dose of FOLOTYN, mean exposures of the pralatrexate S-diastereomer and R- diastereomer were comparable in patients with mild to moderate (eGFR 30 to 59 mL/min/1.73 m^2 based on MDRD) renal impairment as compared with severe (eGFR 15 to 29 mL/min/1.73 m^2) renal impairment. The mean fraction of the administered dose excreted as unchanged diastereomers in urine (fe) decreased with declining renal function [see Use in Specific Populations (8.6)].

Drug Interaction Studies

Clinical Studies
Coadministration of probenecid (an inhibitor of multidrug resistance-associated protein 2 [MRP2] in vitro) resulted in delayed clearance of pralatrexate.

In Vitro Studies

Cytochrome P450 (CYP) Enzymes: Pralatrexate does not induce or inhibit CYP enzymes.

Transporter Systems: Pralatrexate is a substrate for BCRP, MRP2, MRP3, and OATP1B3, but is not a substrate of P-gp, OATP1B1, OCT2, OAT1, or OAT3.

Pralatrexate inhibits MRP2 and MRP3, but does not inhibit P-gp, BCRP, OCT2, OAT1, OAT3, OATP1B1, or OATP1B3. MRP3 is a transporter that may affect the transport of etoposide and teniposide.

13 NONCLINICAL TOXICOLOGY

13.1 Carcinogenesis, Mutagenesis, Impairment of Fertility

Carcinogenesis
Carcinogenicity studies have not been performed with pralatrexate.

Mutagenesis
Pralatrexate did not cause mutations in the Ames test or the Chinese hamster ovary cell chromosome aberration assay. Nevertheless, these tests do not reliably predict genotoxicity for this class of compounds. Pralatrexate did not cause mutations in the mouse micronucleus assay.

Impairment of Fertility
No fertility studies have been performed.

14 CLINICAL STUDIES

The efficacy of FOLOTYN was evaluated in Study PDX-008, an open-label, single-arm, multi-center, international trial that enrolled patients with relapsed or refractory PTCL. One hundred and eleven patients received FOLOTYN 30 mg/m^2 intravenously over 3 to 5 minutes once weekly by for 6 weeks in 7-week cycles until disease progression or unacceptable toxicity. Of the 111 patients treated, 109 patients were evaluable for efficacy. Evaluable patients had histologically confirmed PTCL by independent central review using the Revised European American Lymphoma (REAL) World Health Organization (WHO) disease classification, and relapsed or refractory disease after at least one prior treatment.

The major efficacy outcome measure was overall response rate (complete response, complete response unconfirmed, and partial response) as assessed by International Workshop Criteria (IWC). An additional efficacy outcome measure was duration of response. Response assessments were scheduled at the end of cycle 1 and then every other cycle (every 14 weeks). Duration of response was measured from the first day of documented response to disease progression or death. Response and disease progression were evaluated by independent central review using the IWC.
The median age was 59 years (range: 21 to 85); 68% were male; 72% were White, 13% were Black, 8% were Hispanic and 5% were Asian. Patients had a baseline Eastern Cooperative Oncology Group (ECOG) performance status of 0 (39%), 1 (44%), or 2 (17%). The median time from initial diagnosis to study entry was 1.3 years (range 24 days to 26.8 years). The median number of prior systemic therapies was 3 (range 1 to 12). Approximately 24% of patients (n = 27) did not have evidence of response to any previous therapy. Approximately 63% of patients (n = 70) did not have evidence of response to their most recent prior therapy before entering the study.
Efficacy results are provided in Table 5.

Table 5 Efficacy Results for Study PDX-008 per Independent Central Review (IWC)
 | Evaluable Patients (N=109)
 | N (%) | 95% CI | Median Duration of Response | Range of Duration of Response
Overall Response
CR+CRu+PR | 29 (27) | 19, 36 | 287 days (9.4 months) | 1-503 days
CR/CRu | 9 (8)
PR | 20 (18)
Responses ≥ 14 weeks
CR+CRu+PR | 13 (12) | 7, 20 | Not Reached | 98-503 days
CR/CRu | 7 (6)
PR | 6 (6)

Fourteen patients went off treatment in cycle 1; 2 patients were unevaluable for response by IWC due to insufficient materials provided to central review.
CR = Complete Response, CRu = Complete Response unconfirmed, PR = Partial Response

The initial response assessment was scheduled at the end of cycle 1. Of the responders, 66% responded within cycle 1. The median time to first response was 45 days (range 37-349 days).

15 REFERENCES

1. “OSHA Hazardous Drugs.” OSHA. http://www.osha.gov/SLTC/hazardousdrugs/index.html.

16 HOW SUPPLIED/STORAGE AND HANDLING

FOLOTYN is available in clear glass single-dose vials containing pralatrexate at a concentration of 20 mg/mL as a preservative-free, sterile, clear yellow solution individually packaged for intravenous use in the following presentations:

NDC 72893-003-01: 20 mg of pralatrexate in 1 mL solution in a vial (20 mg / 1 mL)

NDC 72893-005-01: 40 mg of pralatrexate in 2 mL solution in a vial (40 mg / 2 mL)

Store refrigerated at 2-8°C (36-46°F) [see USP Controlled Cold Temperature] in original carton to protect from light.
FOLOTYN is a hazardous drug. Follow applicable special handling and disposal procedures.^1

17 PATIENT COUNSELING INFORMATION

Advise the patient to read the FDA-approved patient labeling (Patient Information).

Folic Acid and Vitamin B12 Supplementation
Advise patients treated with FOLOTYN to take folic acid and vitamin B12 to reduce the risk of possible side effects [see Dosage and Administration (2.1)].

Myelosuppression
Inform patients of the risk of myelosuppression and to immediately contact their healthcare provider should any signs of infection develop, including fever. Inform patients to contact their healthcare provider if bleeding or symptoms of anemia occur [see Warnings and Precautions (5.1)].

Mucositis
Inform patients of the signs and symptoms of mucositis. Instruct patients on ways to reduce the risk of its development, and on ways to maintain nutrition and control discomfort from mucositis if it occurs [see Warnings and Precautions (5.2)].

Dermatologic Reactions
Advise patients about the risks for and the signs and symptoms of dermatologic reactions. Instruct patients to immediately notify their healthcare provider if any skin reactions occur [see Warnings and Precautions (5.3)].

Tumor Lysis Syndrome
Inform patients about the risk of and the signs and symptoms of tumor lysis syndrome. Patients should be instructed to notify their healthcare provider if they experience these symptoms [see Warnings and Precautions (5.4)].

Concomitant Medications
Patients should be instructed to inform their healthcare provider if they are taking any concomitant medications including prescription drugs (such as trimethoprim/sulfamethoxazole and probenecid) and nonprescription drugs (such as nonsteroidal anti-inflammatory drugs) [see Drug Interactions (7.1)].

Embryo-Fetal Toxicity
Advise pregnant women and females of reproductive potential of the potential risk to a fetus. Advise females or reproductive potential to inform their healthcare provider of a known or suspected pregnancy [see Warnings and Precautions (5.7) and Use in Specific Populations (8.1)].

Advise females patients of reproductive potential to use effective contraception during treatment with FOLOTYN and for 6 months after the final dose [see Use in Specific Populations (8.3)].

Advise males with female partners of reproductive potential to use effective contraception during treatment with FOLOTYN and for at least 3 months after the final dose [see Use in Specific Populations (8.3)]

Lactation
Advise females women not to breastfeed during treatment with FOLOTYN and for 1 week after the final dose [see Use in Specific Populations (8.2)].

Manufactured by:
Baxter Oncology GmbH
Halle, 33790, Germany

Manufactured for:
Acrotech Biopharma Inc
East Windsor, NJ 08520 USA
1-888-255-6788
FOLOTYN is a registered trademark of Acrotech Biopharma Inc. U.S.

Patents: 6,028,071, 7,622,470 and 8,299,078
© Acrotech Biopharma Inc. All rights reserved.

SPL PATIENT PACKAGE INSERT SECTION

Patient Information

FOLOTYN® (FOH-loh-tin)
(pralatrexate injection)

What is FOLOTYN?

FOLOTYN is a prescription used to treat people with a type of cancer called peripheral T-cell lymphoma (PTCL) that does not go away, gets worse, or comes back after use of another cancer treatment. It is not known if FOLOTYN is safe and effective in children.

Before you receive FOLOTYN, tell your healthcare provider about all of your medical conditions, including if you:

- have kidney problems, including end-stage renal disease (ESRD)

- are pregnant or plan to become pregnant. FOLOTYN can harm your unborn baby.
  Females who are able to become pregnant:
  - Your healthcare provider may do a pregnancy test before you start treatment with FOLOTYN.
  - You should use effective birth control (contraception) during treatment with FOLOTYN and for 6 months after the last dose. Talk to your healthcare provider about the best birth control methods you can use during this time.
  - Tell your healthcare provider if you become pregnant or think you may be pregnant during treatment with FOLOTYN.
  Males with female partners who are able to become pregnant should use effective birth control during treatment with FOLOTYN and for 3 months after the last dose of FOLOTYN.

- are breastfeeding or plan to breastfeed. It is not known if FOLOTYN passes into your breast milk. Do not breastfeed during treatment with FOLOTYN and for 1 week after the last dose. Talk to your healthcare provider about the best way to feed your baby during treatment with FOLOTYN.

Tell your healthcare provider about all the medicines you take, including prescription and over-the-counter medicines, vitamins, and herbal supplements. Some medicines may affect how FOLOTYN works.

Especially tell your healthcare provider if you take:

- sulfamethoxazole trimethoprim
- non-steroidal anti-inflammatory drugs (NSAIDs) medicines
- probenecid

Know the medicines you take. Keep a list of them and show it to your healthcare provider or pharmacist each time you start a new medicine.

How will I receive FOLOTYN?

- FOLOTYN will be given to you by your healthcare provider as an intravenous (IV) injection into your vein over 3 to 5 minutes.
- FOLOTYN is usually given in cycles, one time each week for 6 weeks, with no treatment on the 7th week.
- Your healthcare provider will treat you with folic acid and vitamin B12 before and during your treatment with FOLOTYN to help reduce the risk of possible side effects.
  - You will take folic acid by mouth for 10 days before your first dose of FOLOTYN. Continue taking folic acid during treatment with FOLOTYN and for 30 days after the last dose.
  - Your healthcare provider will give you a vitamin B12 injection into your muscle (intramuscular). You will get your first vitamin B12 injection 10 weeks before your first dose of FOLOTYN and every 8 to 10 weeks during treatment with FOLOTYN.

- Your healthcare provider will do blood tests before and during treatment with FOLOTYN.

Your healthcare provider may stop treatment, delay treatment, or change your dose of FOLOTYN based on results of your blood tests and if you have certain side effects.

What are the possible side effects of FOLOTYN?
FOLOTYN may cause serious side effects, including:

- Low blood cell counts: Your healthcare provider will do blood tests to check your blood cell counts before and during treatment with FOLOTYN. Tell your healthcare provider right away if you develop any signs of infection, fever, bleeding or tiredness during treatment with FOLOTYN.
- Redness and sores of the mucous membrane lining of the mouth, lips, throat, digestive tract, and genitals (mucositis). Mucositis is common with FOLOTYN and can be severe. Tell your healthcare provider if you develop redness or painful sores in your mouth or throat, or have trouble speaking, eating or drinking. Your healthcare provider will tell you about ways to reduce your risk of getting mucositis, and how to maintain nutrition and help control the discomfort from mucositis.
- Severe skin reactions. FOLOTYN can cause severe skin reactions that may lead to death. In people with lymphoma, severe skin reactions may happen on and under your skin. Tell your healthcare provider right away if you develop any f the following skin reactions:
  - rash
  - peeling and loss of skin
  - sores
  - blisters

- Tumor Lysis Syndrome (TLS). TLS is caused by the fast breakdown of certain types of cancer cells. Your healthcare provider may do blood tests to check you for TLS and treat you if needed.
- Liver problems. Your healthcare provider will monitor you for liver problems during treatment with FOLOTYN.
- Increased risk of serious reactions in people with kidney problems. People with severe kidney problems may have a greater risk for increased serious reactions during treatment with FOLOTYN.

The most common side effects of FOLOTYN include: low platelet blood counts, nausea, and tiredness.

These are not all of the possible side effects of FOLOTYN.
Call your doctor for medical advice about side effects. You may report side effects to FDA at 1-800-FDA-1088.

General information about the safe and effective use of FOLOTYN.
Medicines are sometimes prescribed for purposes other than those listed in a Patient Information leaflet. This Patient Information leaflet summarizes the most important information about FOLOTYN. If you would like more information, talk with your healthcare provider. You can ask your healthcare provider or pharmacist for information about FOLOTYN that is written for health professionals.

What are the ingredients in FOLOTYN?

Active ingredient:pralatrexate

Inactive ingredients:sodium chloride, sodium hydroxide, and hydrochloric acid

Manufactured by:
Baxter Oncology GmbH
Halle, 33790, Germany

Manufactured for:

Acrotech Biopharma Inc
East Windsor, NJ 08520 USA

FOLOTYN and the flower symbol are all registered trademarks of Acrotech Biopharma Inc.

© Acrotech Biopharma Inc. All rights reserved.

For more information, go to www.FOLOTYN.com or call 1-888-255-6788.

This Patient Information has been approved by the U.S. Food and Drug Administration Revised: Aug 2024

PACKAGE LABEL.PRINCIPAL DISPLAY PANEL

PACKAGE CARTON - FOLOTYN 20 mg/1 mL Vial

NDC 72893-003-01
FOLOTYN®

(pralatrexate injection)

20 mg/mL

For intravenous use

Rx only

1 mL

PACKAGE LABEL.PRINCIPAL DISPLAY PANEL

PACKAGE CARTON - FOLOTYN 40 mg/2 mL Vial

NDC 72893-005-01

FOLOTYN®

(pralatrexate injection)

40 mg/2 mL

(20 mg/mL)

For intravenous use

Rx only

2 mL

PACKAGE LABEL.PRINCIPAL DISPLAY PANEL

VIAL – FOLOTYN 20 mg/1 ml

NDC 72893-003-01

FOLOTYN®

(pralatrexate injection)

20 mg/mL

Rx only

1 mL

PACKAGE LABEL.PRINCIPAL DISPLAY PANEL

VIAL – FOLOTYN 40 mg/2 ml

NDC 72893-005-01

FOLOTYN®

(pralatrexate injection)

40 mg/2 mL
(20 mg/mL)

Rx only

2 mL